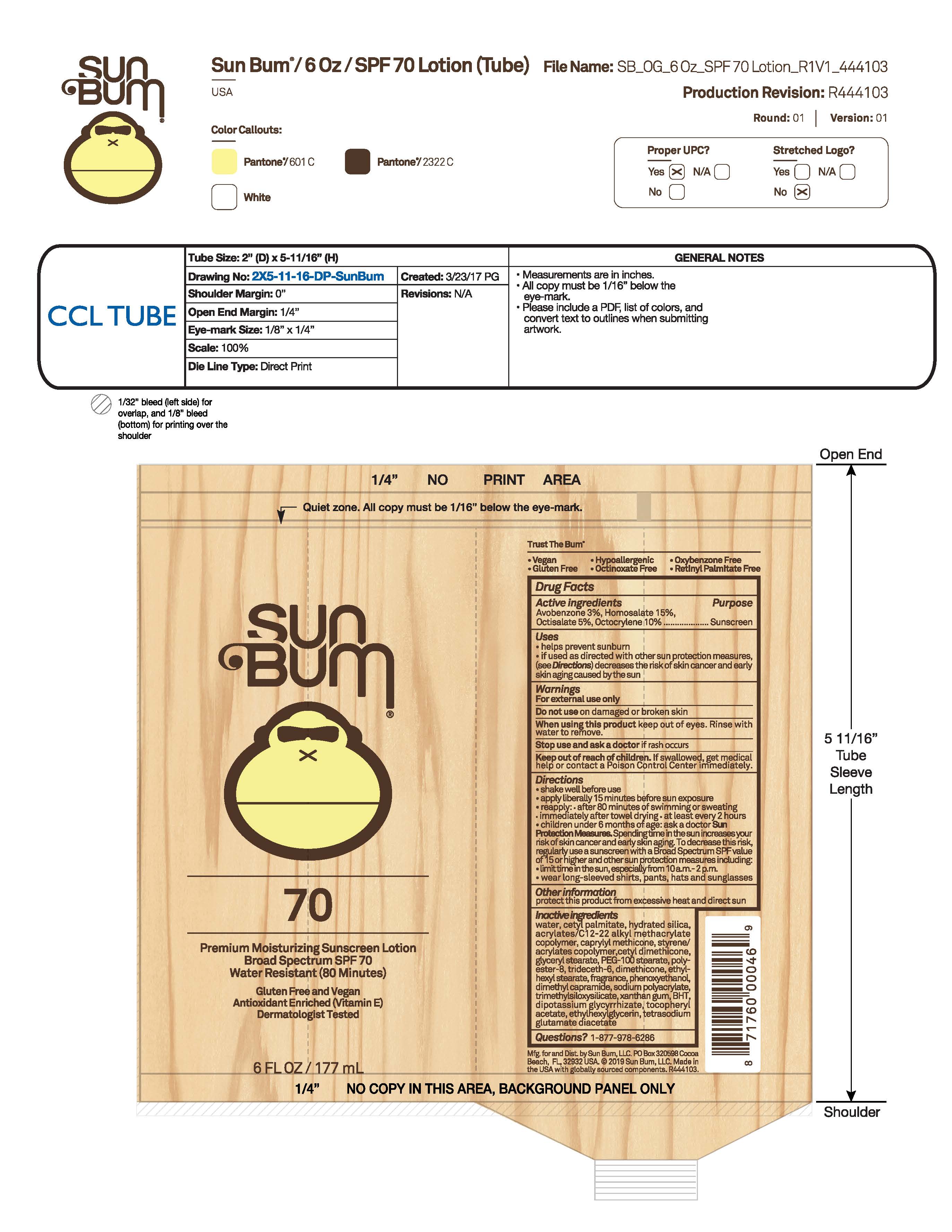 DRUG LABEL: Sun Bum 70 Premium Moisturizing Sunscreen
NDC: 69039-793 | Form: LOTION
Manufacturer: Sun Bum, LLC
Category: otc | Type: HUMAN OTC DRUG LABEL
Date: 20250826

ACTIVE INGREDIENTS: AVOBENZONE 30 mg/1 mL; OCTISALATE 50 mg/1 mL; OCTOCRYLENE 100 mg/1 mL; HOMOSALATE 150 mg/1 mL
INACTIVE INGREDIENTS: CETYL DIMETHICONE 25; CAPRYLYL METHICONE; LUVISET 360; DIMETHICONE; TRIMETHYLSILOXYSILICATE (M/Q 0.6-0.8); TRIDECETH-6; ETHYLHEXYL STEARATE; ETHYLHEXYLGLYCERIN; WATER; ACRYLATES/C10-30 ALKYL ACRYLATE CROSSPOLYMER (60000 MPA.S); DIMETHYL CAPRAMIDE; GLYCERYL STEARATE; PHENOXYETHANOL; PEG-100 STEARATE; SODIUM POLYACRYLATE (8000 MW); DIPOTASSIUM GLYCYRRHIZATE; XANTHAN GUM; TETRASODIUM GLUTAMATE DIACETATE; CETYL PALMITATE; HYDRATED SILICA; .ALPHA.-TOCOPHEROL ACETATE; BHT; POLYESTER-8 (1400 MW, CYANODIPHENYLPROPENOYL CAPPED)

Sun Bum 70 Premium Moisturizing Sunscreen

Active Ingredients

Avobenzone 3.0%, Homosalate 15.0%, Octisalate 5.0%, Octocrylene 10.0%

Purpose

Sunscreen

Uses

• helps prevent sunburn • if used as directed with other sun protection measures, (see Directions) decreases the risk of skin cancer and early skin aging caused by the sun

Warnings

For external use only

Do not use on damaged or broken skin

When using this product keep out of eyes. Rinse with water to remove.

Stop use and ask a doctor if rash occurs

Keep out of reach of children. If swallowed, get medical help or contact a Poison Control Center immediately.

Warnings

Keep Out Of Reach Of Children

Directions

• shake well before use

• apply liberally 15 minutes before sun exposure

• reapply: • after 80 minutes of swimming or sweating • immediately after towel drying • at least every 2 hours

• children under 6 months of age: ask a doctor

• Sun Protection Measures. Spending time in the sun increases your risk of skin cancer and early skin aging. To decrease this risk, regularly use a sunscreen with a Broad Spectrum SPF value of 15 or higher and other sun protection measures including:

• limit time in the sun, especially from 10 a.m.- 2 p.m.

• wear long-sleeved shirts, pants, hats and sunglasses

Directions

• shake well before use

• apply liberally 15 minutes before sun exposure

Other Information

protect this product from excessive heat and direct sun

Inactive Ingredients

water, cetyl palmitate, hydrated silica, acrylates/C12-22 alkyl methacrylate copolymer, caprylyl methicone, styrene/acrylates copolymer, cetyl dimethicone, glyceryl stearate, PEG-100 stearate, polyester-8, trideceth-6, dimethicone, ethylhexyl stearate, fragrance, phenoxyethanol, dimethyl capramide, sodium polyacrylate, trimethylsiloxysilicate, xanthan gum, BHT, dipotassium glycyrrhizate, tocopheryl acetate, ethylhexylglycerin, tetrasodium glutamate diacetate

Questions?

1-877-978-6286